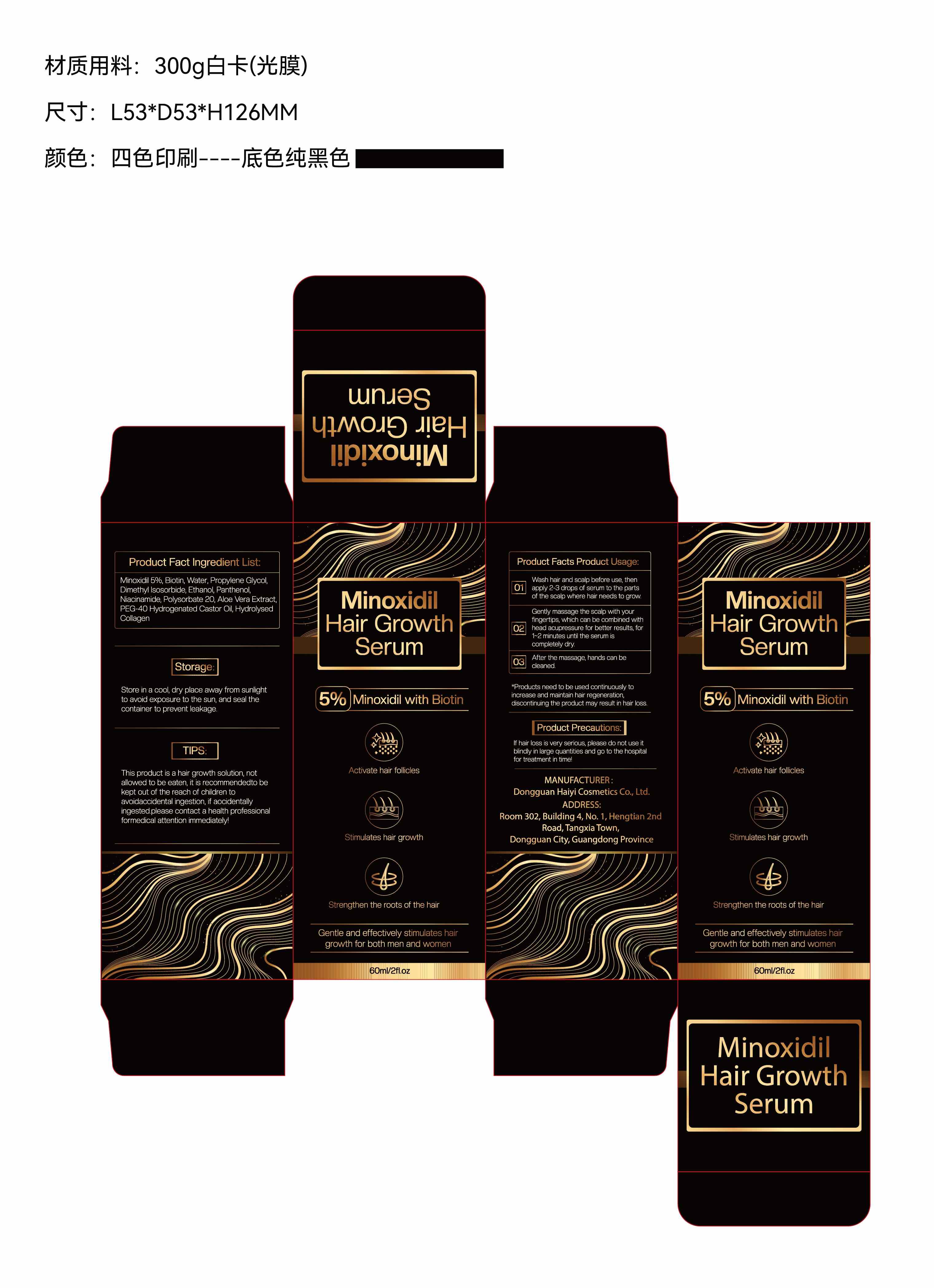 DRUG LABEL: Minoxidi Hair Growth Serum
NDC: 85594-001 | Form: LIQUID
Manufacturer: Dongguan Haiyi Cosmetics Co., Ltd.
Category: otc | Type: HUMAN OTC DRUG LABEL
Date: 20250504

ACTIVE INGREDIENTS: MINOXIDIL 5 mg/60 mL
INACTIVE INGREDIENTS: PANTHENOL; NIACINAMIDE; POLYSORBATE 20; BIOTIN; PEG-40 HYDROGENATED CASTOR OIL; PROPYLENE GLYCOL; DIMETHYL ISOSORBIDE; HYDROLYSED BOVINE COLLAGEN (ENZYMATIC; 2000-5000 MW); ALCOHOL; WATER; ALOE VERA LEAF

85594-001-01 MINOXIDI HAIR GROWTH SERUM

ACTIVE INGREDIENT

Minoxidil 5%

PURPOSE

1.Reactivates Hair Follicles
2.Grow Stronger and Thicker Hair
3.Help Regrow Hair

WHEN USING

1.Apply 2-3 drops of serum directly tothescalp in the area to be treated.
2.Massage into the scalp with yourfngersthen wash hands thoroughly.
3.Using more hair regrowth serumorusing the serum more often willnotimprove your
results.
4.Continued use is necessary to increaseand then maintain your hair regrowth.
5.Discontinuing use may result inhair loss.

DOSAGE AND ADMINISTRATION

lt takes time to regrow hairYou mayneed to use this product 2times a day forat least 4
months beforeyou see results,The amount of hair regrowth is different for each
person.The product will not work for everyone.

WARNINGS

Do not apply on other parts ofthe body Avoid contact with eyes. In case ofaccidental
contact, rinse eyes witha large amount of cool tap water.

INDICATIONS AND USAGE

1.Apply 2-3 drops of serum directly tothescalp in the area to be treated.
2.Massage into the scalp with yourfngersthen wash hands thoroughly.
3.Using more hair regrowth serumorusing the serum more often willnotimprove your
results.
4.Continued use is necessary to increaseand then maintain your hair regrowth.
5.Discontinuing use may result inhair loss.

STOP USE

This product may cause allergic reactions in asmall number of people.
lf youexperience any discomfort,please stop using it immediately

KEEP OUT OF REACH OF CHILDREN

Not suitable for use by children, pregnantor breast feeding people. keep out of reach of children

INACTIVE INGREDIENT

Biotin,Water, Propylene Glycol, Dimethyl lsosorbide, Ethanol, Panthenol,Niacinamide, Polysorbate 20, Aloe Vera Extract,PEG-40 Hydrogenated castor Oil, HydrolysedCollagen